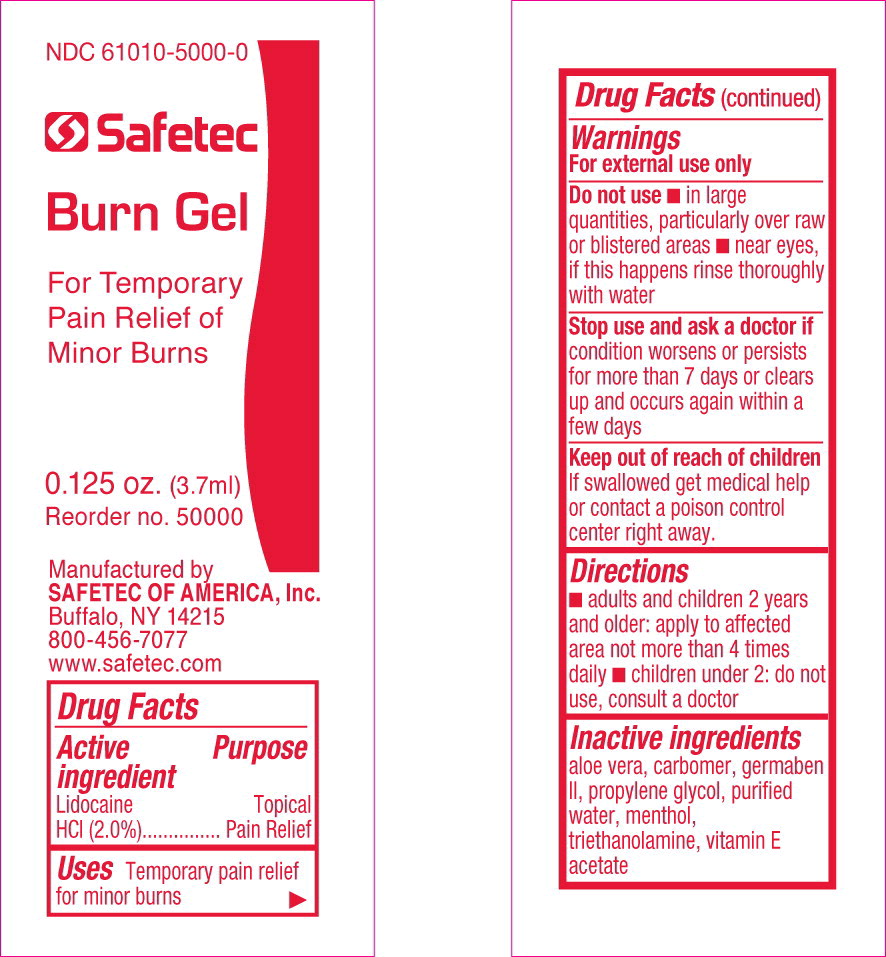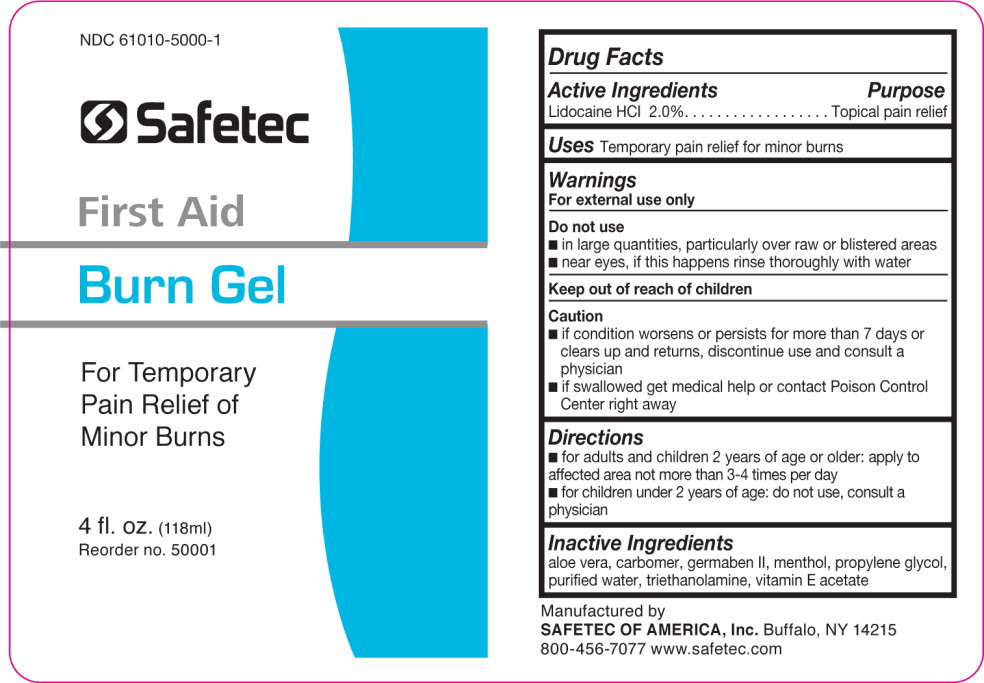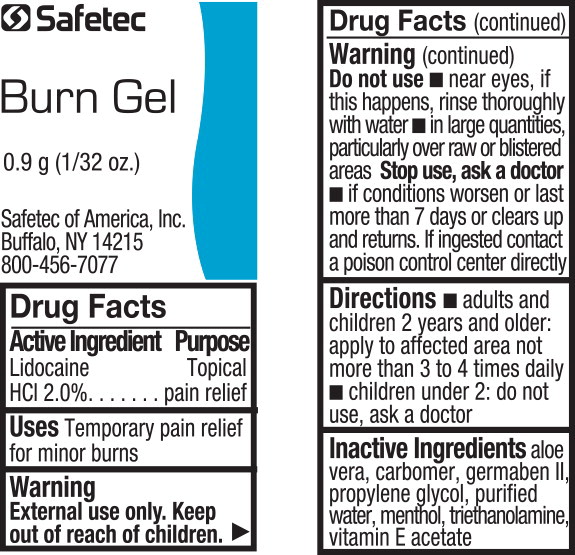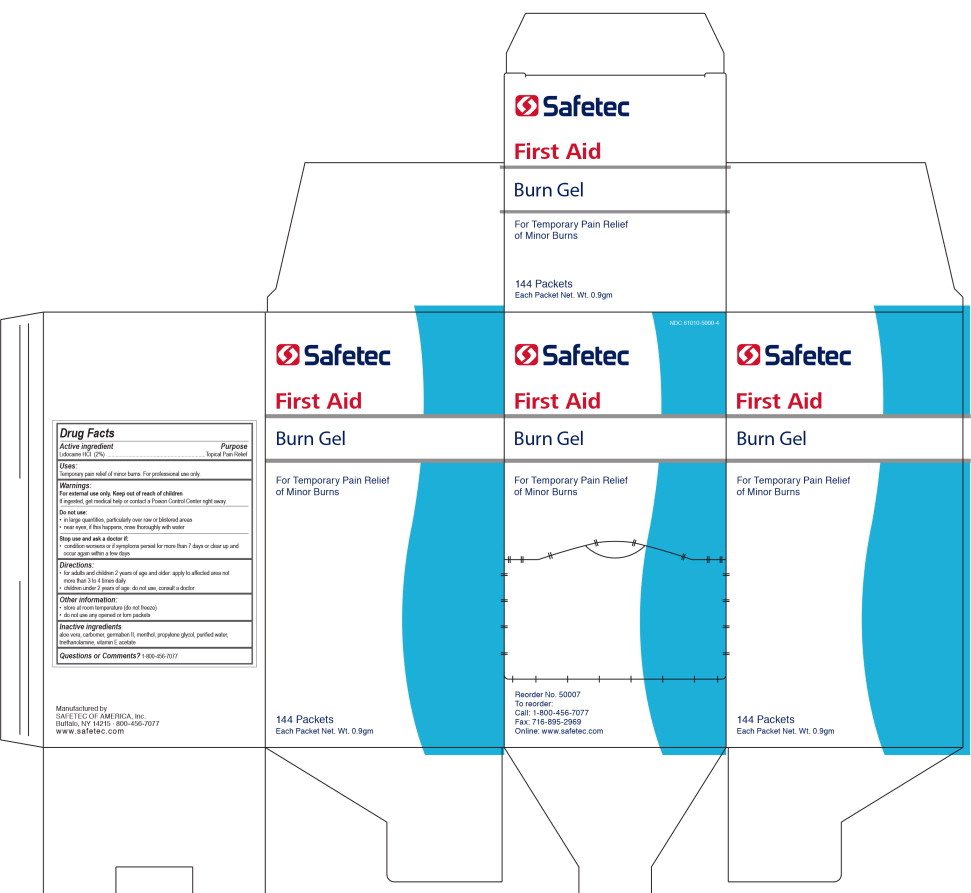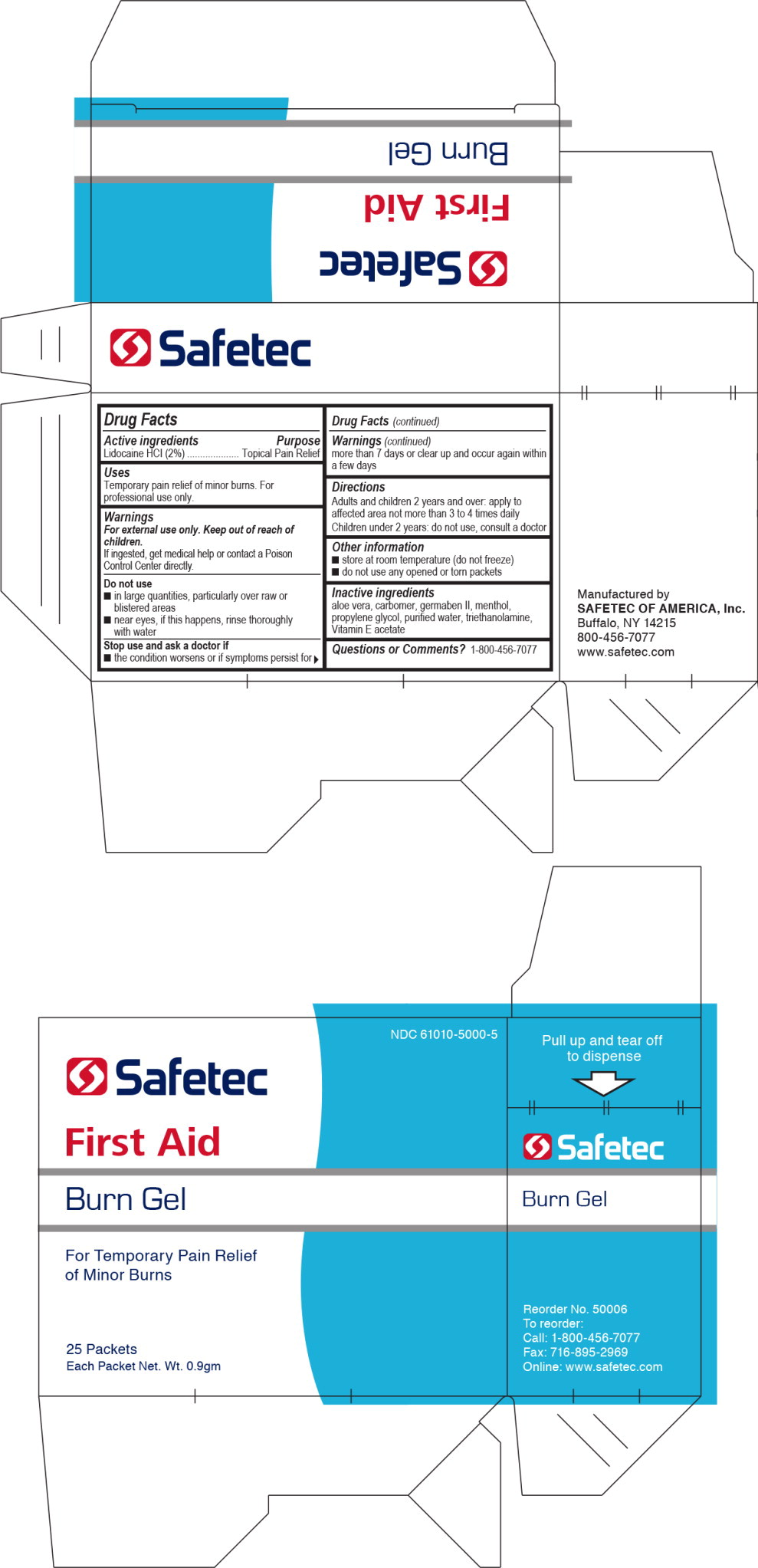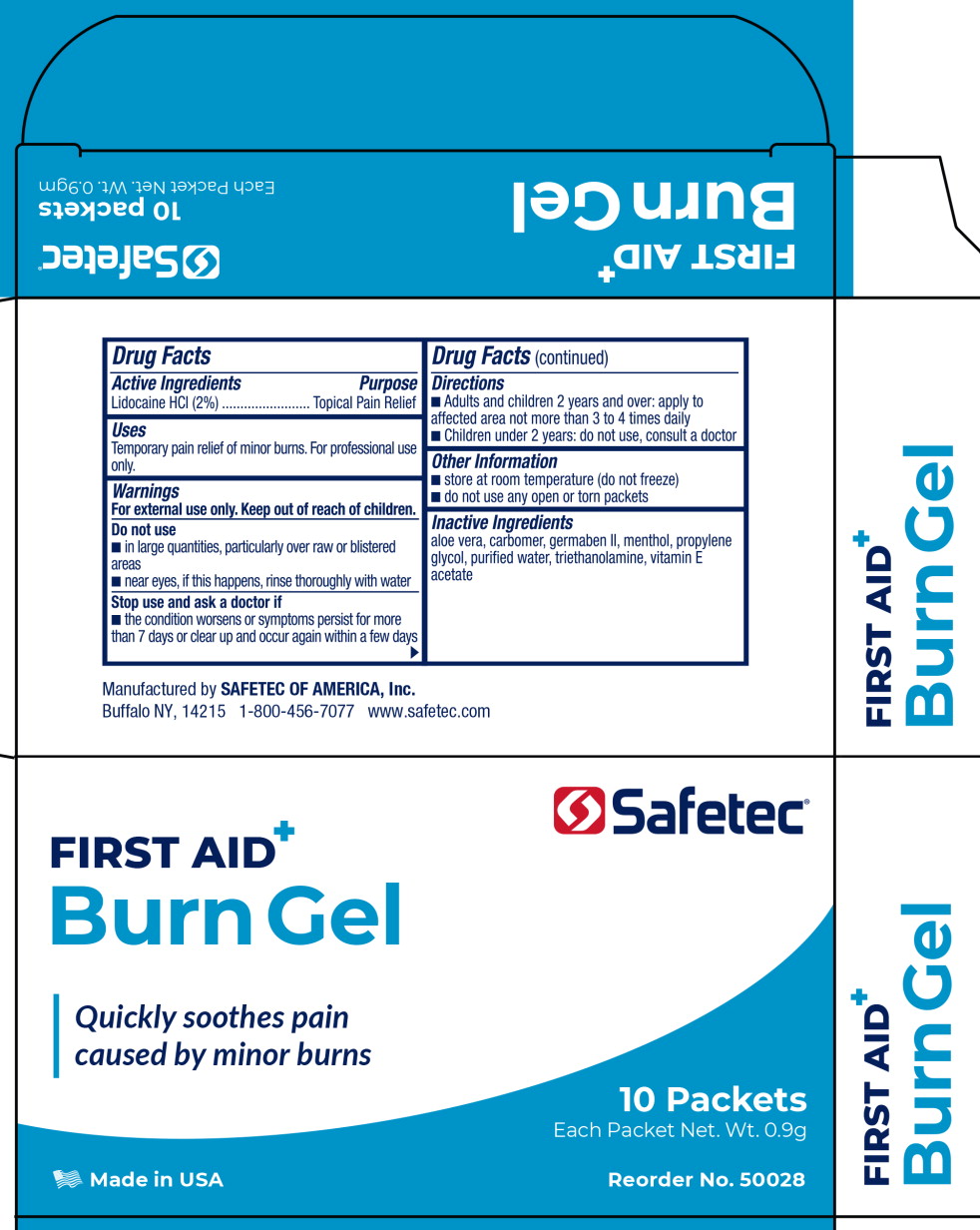 DRUG LABEL: Lidocaine Hydrochloride
NDC: 61010-5000 | Form: GEL
Manufacturer: Safetec of America, Inc.
Category: otc | Type: HUMAN OTC DRUG LABEL
Date: 20240207

ACTIVE INGREDIENTS: LIDOCAINE HYDROCHLORIDE 20 mg/1 g
INACTIVE INGREDIENTS: ALOE VERA LEAF; PROPYLENE GLYCOL; DIAZOLIDINYL UREA; WATER; MENTHOL; .ALPHA.-TOCOPHEROL ACETATE; TROLAMINE

61010-5000, Burn Gel

Pain Relief

Drug Facts

Active Ingredient

Lidocaine HCl 2.0%

Purpose

Topical pain relief

Uses

Temporary pain relief for minor burns

Warnings

For external use only

Do not use

- In large quantities, particularly over raw or blistered areas
- near eyes, if this happens rinse thoroughly with water

Stop use and ask doctorif condition worsens or persists for more than 7 days or clears up and occurs again within a few days

Keep out of reach of children.

If swallowed get medical help or contact a Poison Control Center right away

Directions

- for adults and children 2 years and older: apply to affected area not more than 4 times daily
- children under 2: do not use, consult a doctor

Inactive ingredients

aloe vera, carbomer, germaben II, propylene glycol, purified water, menthol, triethanolamine, vitamin E acetate

PRINCIPAL DISPLAY PANEL – 0.125 oz. packet

NDC 61010-5000-0

Safetec

Burn Gel

For Temporary
Pain Relief of
Minor Burns

0.125 oz. (3.7 ml)
Reorder no. 50000

Manufactured by
SAFETEC OF AMERICA, Inc.
Buffalo, NY 14215
800-456-7077
www.safetec.com

PRINCIPAL DISPLAY PANEL – 4 oz. bottle

NDC 61010-5000-1

Safetec

First Aid
Burn Gel

For Temporary
Pain Relief of
Minor Burns

4 fl. oz. (118 ml)
Reorder no. 50001

Principal Display Panel - Pouch label

Safetec

Burn Gel

0.9 g (1/32 oz.)

Safetec of America, Inc.

Buffalo, NY 14215

800-456-7077

Principal Display Panel - 144 Box label

NDC 61010-5000-04

Safetec

First Aid

Burn Gel

For Temporary Pain Relief
of Minor Burns

Reorder No. 50007

To reorder:

Call: 1-800-456-7077

Fax: 716-895-2969

Online: www.safetec.com

Principal Display Panel - 25 Box label

NDC 61010-5000-5

Safetec

First Aid

Burn Gel

For Temporary Pain Relief
of Minor Burns

25 Packets

Each Packet Net. Wt. 0.9gm

Principal Display Panel – 10 Packet Box Label

Safetec®

First Aid

Burn Gel

Quickly soothes pain
caused by minor burns

10 Packets

Each Packet Net. Wt. 0.9g

Made in USA

Reorder No. 50028